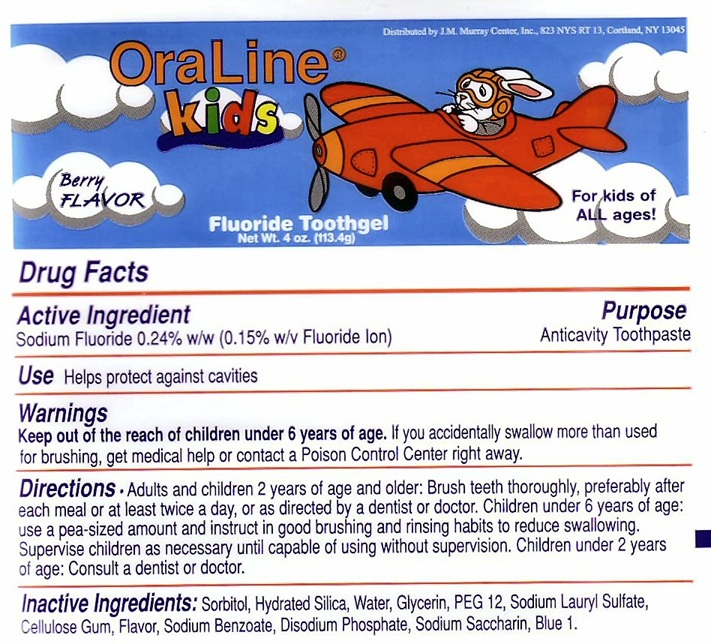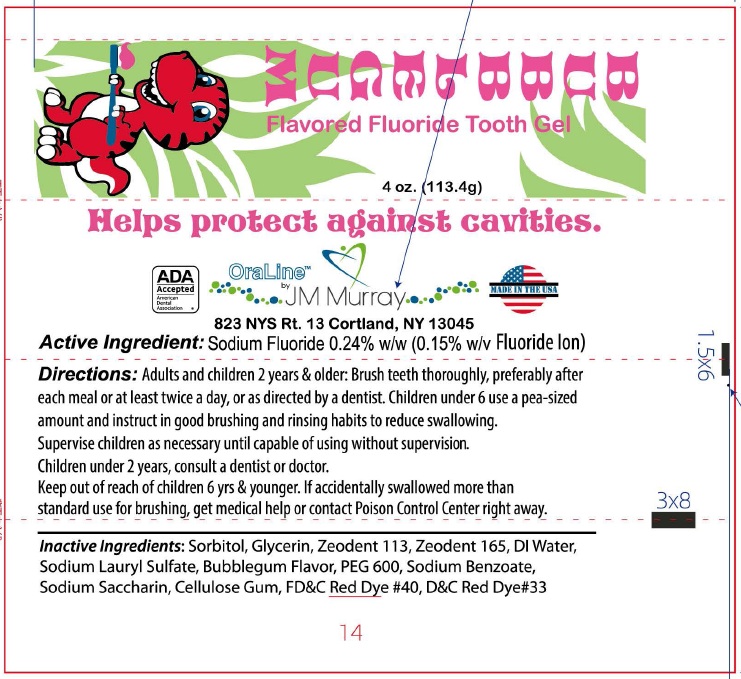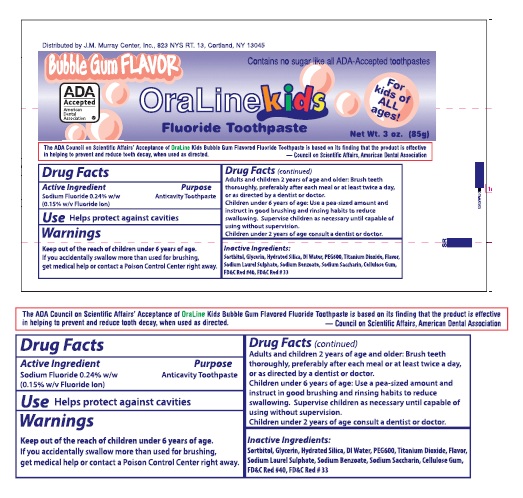 DRUG LABEL: OralLine Kids
NDC: 55873-003 | Form: GEL, DENTIFRICE
Manufacturer: J.M. Murray Center Inc.
Category: otc | Type: HUMAN OTC DRUG LABEL
Date: 20250321

ACTIVE INGREDIENTS: SODIUM FLUORIDE 0.15 g/100 g
INACTIVE INGREDIENTS: SORBITOL; HYDRATED SILICA; WATER; GLYCERIN; POLYETHYLENE GLYCOL 600; SODIUM LAURYL SULFATE; CARBOXYMETHYLCELLULOSE SODIUM; SODIUM BENZOATE; SODIUM PHOSPHATE, DIBASIC, DIHYDRATE; SACCHARIN SODIUM; FD&C BLUE NO. 1

Active Ingredient

Sodium Fluoride 0.24% w/w (0.15% w/v Fluoride Ion)

Inactive Ingredients

Sorbitol, Hydrated Silica, DI Water, Glycerin, PEG 600, Sodium Lauryl Sulfate, Cellulose Gum, Titanium Dioxide, Sodium Saccharin, FD C Blue 1

Purpose

Anticavity Toothpaste

Use

Use - Helps protect against cavities

Directions

Adults and children 2 years of age and older. Brush teeth thoroughly, preferably after each meal or at least twice a day or as directed by a dentist or doctor.

Children under 6 years of age. Use a pea-sized amount and instruct in good brushing and rinsing habits to reduce swallowing. Supervise children as necessary until capable of using without supervision.

Warnings

If you accidentally swallow more than used for brushing get medical help or contact a poison control center immediately.

Keep Out of Reach of Children

Children under 2 years of age consult a doctor or a dentist

Keep out of the reach of children under 6 years of age.

Product Labels

OraLine Kids Fluoride Toothpaste ADA accepted.The ADA Council on Scientific Affairs Acceptance of OraLine Fluoride Mint Toothpaste is based on finding that the product is effective in helping to prevent and reduce tooth decay when used as directed

No animal based ingredients. Berry Flavor Net Wt

res